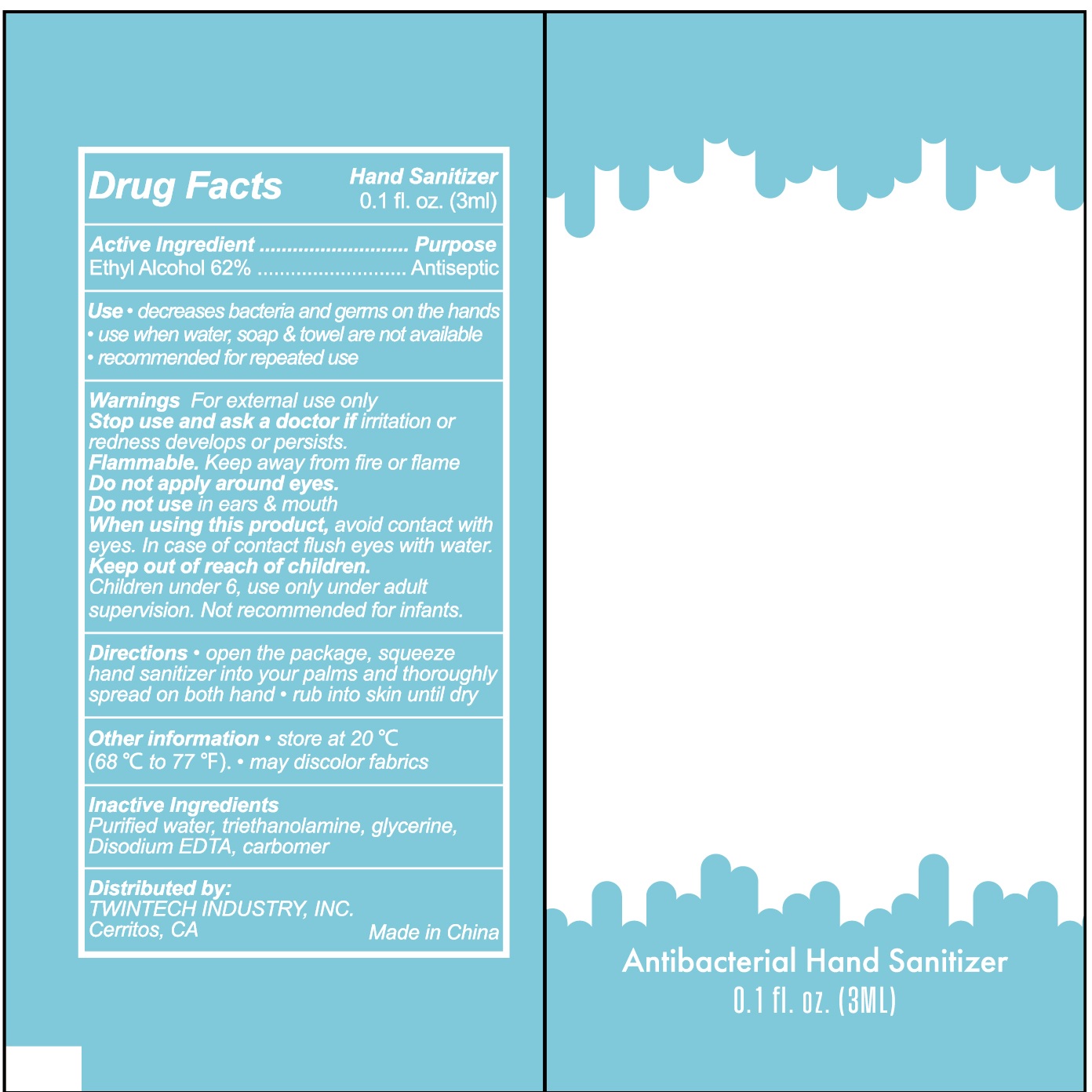 DRUG LABEL: Antibacterial Hnad Sanitizer
NDC: 71734-312 | Form: LIQUID
Manufacturer: JIANGMEN SHUIZIRUN SANITARY ARTICLES CO., LTD.
Category: otc | Type: HUMAN OTC DRUG LABEL
Date: 20200616

ACTIVE INGREDIENTS: ALCOHOL 62 mL/100 mL
INACTIVE INGREDIENTS: GLYCERIN; CARBOMER 934; WATER; TROLAMINE; EDETATE DISODIUM

Drug Fact

Active Ingredient

Ethyl Alcohol 62%

Purpose

Antiseptic

Uses

- decrease bacteria and germs on the hands
- use when soap , towel and water are not available.
- recommended for repeared use.

Warnings

For external use only.

Stop use and ask a doctor ifirritation or redness develops or persists.

Flammable, keep away from fire or flame

Do not apply around eyes.

Do not use in ears and mouth

Other information:

- store at 20℃ (68 to 77 ℉)
- may discolor fabrics

WHEN USING

avoid contact with eyes. In case of contact flush eyes with water

consult a physicia

if irritation or redness develops or persists

Keep out of reach of children.

Children under 6, use only under adult supervision. Not recommended for infants.

Directions

- open the package, squeeze hand sanitizer into your palms and thoroughly spread on both hands
- rub into skin until dry

Inactive Ingredients

purified water, triethanolamine, glycerine, Disodium EDTA, carbomer